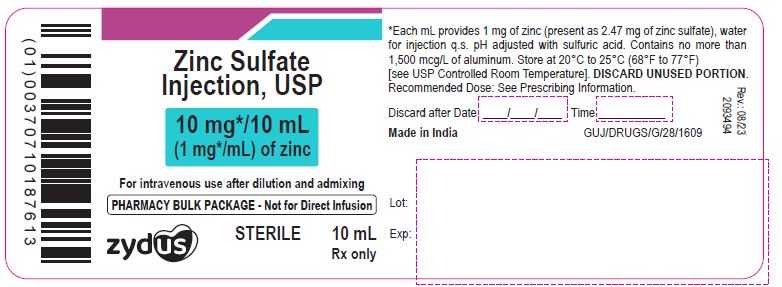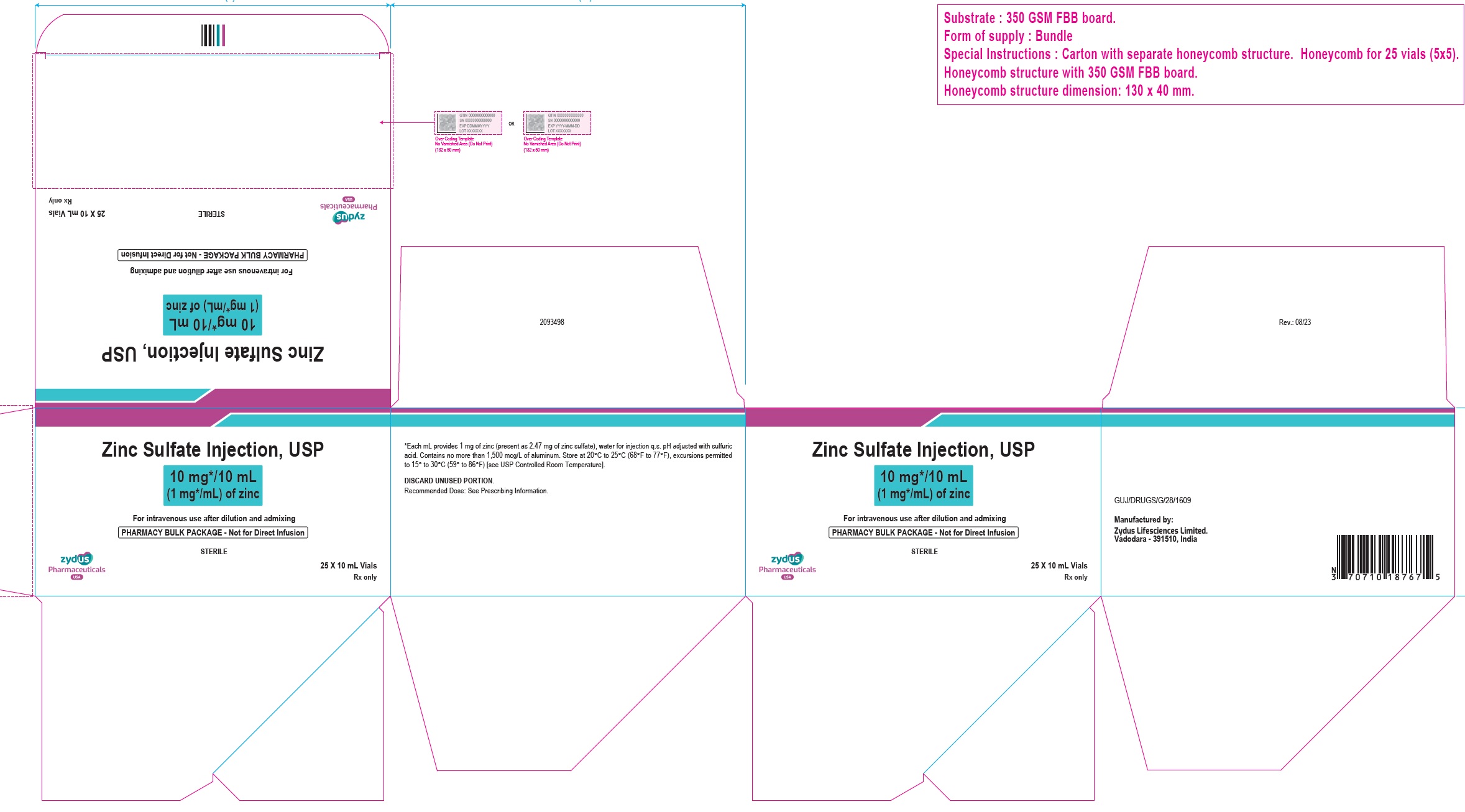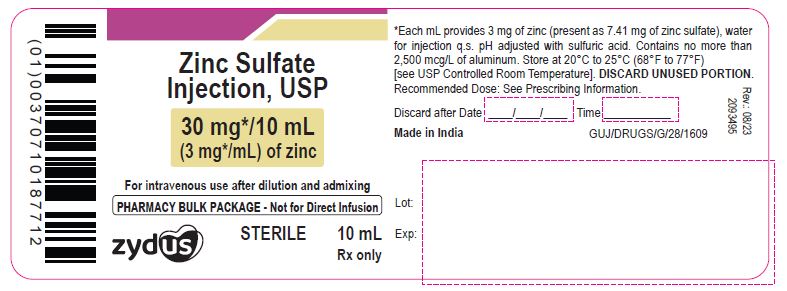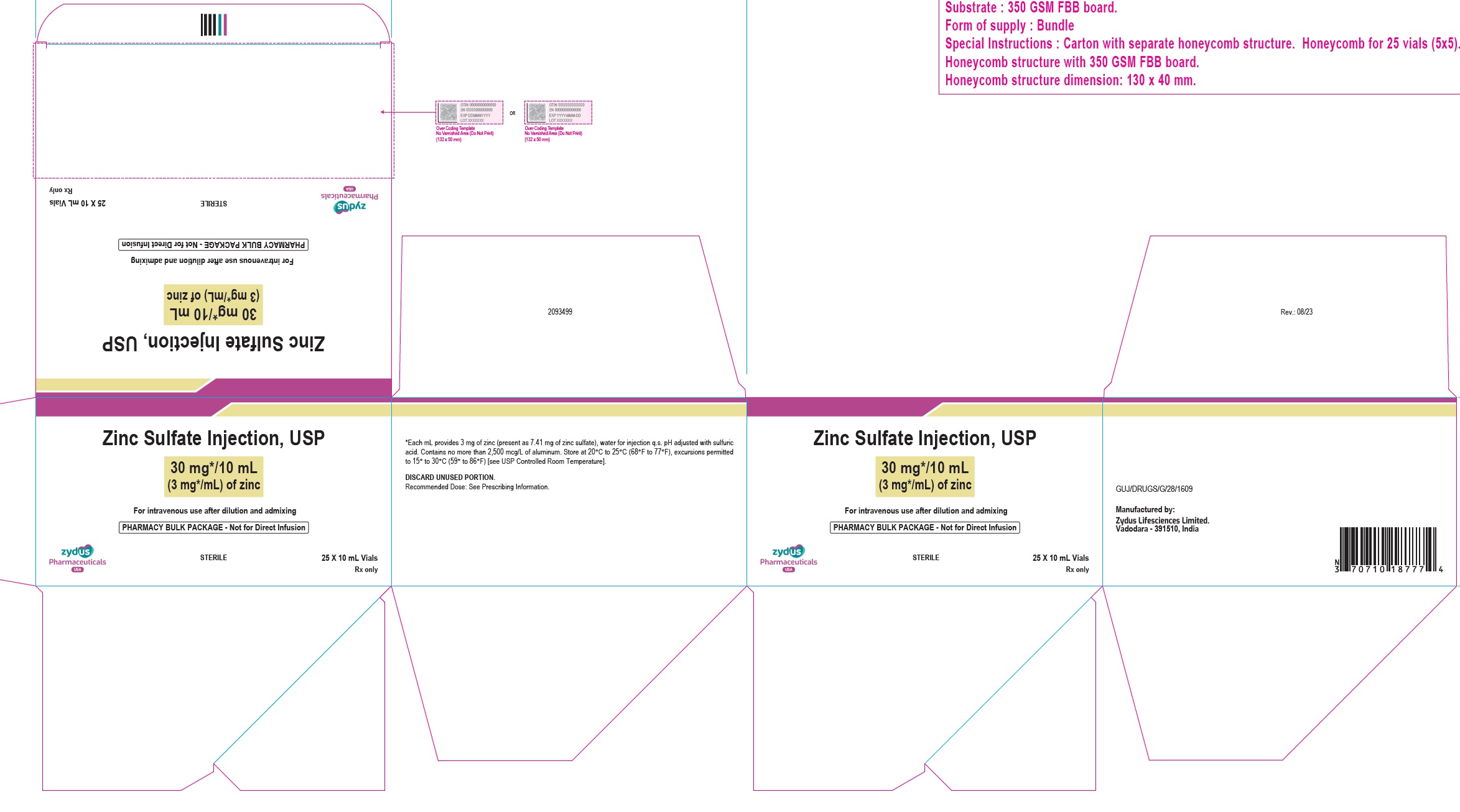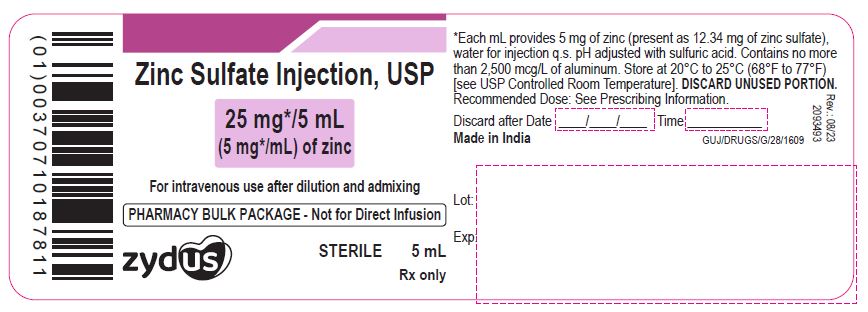 DRUG LABEL: zinc sulfate
NDC: 70771-1848 | Form: INJECTION, SOLUTION
Manufacturer: Zydus Lifesciences Limited
Category: prescription | Type: HUMAN PRESCRIPTION DRUG LABEL
Date: 20230831

ACTIVE INGREDIENTS: ZINC SULFATE 1 mg/1 mL
INACTIVE INGREDIENTS: SULFURIC ACID; WATER

ZINC SULFATE INJECTION for intravenous use

PACKAGE LABEL.PRINCIPAL DISPLAY PANEL

NDC 70771-1848-1

Zinc Sulfate Injection, USP

10 mg/10 mL (1 mg/mL) of zinc

For intravenous use after dilution and admixing

PHARMACY BULK PACKAGE-Not for Direct Infusion

STERILE

10 mL

Rx only

NDC 70771-1848-7

Zinc Sulfate Injection, USP

10 mg/10 mL (1 mg/mL) of zinc

For intravenous use after dilution and admixing

PHARMACY BULK PACKAGE-Not for Direct Infusion

25 x 10 mL Vials

STERILE

10 mL

Rx only

NDC 70771-1849-1

Zinc Sulfate Injection, USP

30 mg/10 mL (3 mg/mL) of zinc

For intravenous use after dilution and admixing

PHARMACY BULK PACKAGE-Not for Direct Infusion

STERILE

10 mL

Rx only

NDC 70771-1849-7

Zinc Sulfate Injection, USP

30 mg/10 mL (3 mg/mL) of zinc

For intravenous use after dilution and admixing

PHARMACY BULK PACKAGE-Not for Direct Infusion

25 X 10 mL Vials

STERILE

10 mL

Rx only

NDC 70771-1850-1

Zinc Sulfate Injection, USP

25 mg/5 mL (5 mg/mL) of zinc

For intravenous use after dilution and admixing

PHARMACY BULK PACKAGE-Not for Direct Infusion

STERILE

5 mL

Rx only

NDC 70771-1850-7

Zinc Sulfate Injection, USP

25 mg/5 mL (5 mg/mL) of zinc

For intravenous use after dilution and admixing

PHARMACY BULK PACKAGE-Not for Direct Infusion

25 X 5 mL Vials

STERILE

5 mL

Rx only